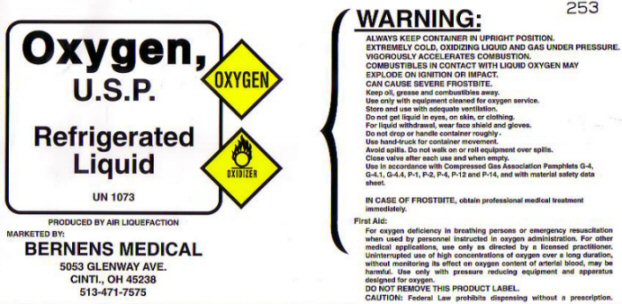 DRUG LABEL: OXYGEN
NDC: 57957-0007 | Form: GAS
Manufacturer: Bernens Convalescent Pharmacy, Inc
Category: prescription | Type: HUMAN PRESCRIPTION DRUG LABEL
Date: 20251216

ACTIVE INGREDIENTS: OXYGEN 99 L/100 L

PRODUCT WARNINGS AND PRECAUTIONS

FIRST AID: FOR OXYGEN DEFICIENCY IN BREATHING PERSONS OR EMERGENCY RESUSCITATION WHEN USED BY PERSONNEL INSTRUCTED IN OXYGEN ADMINISTRATION. FOR OTHER MEDICAL APPLICATIONS USE ONLY AS DIRECTED BY A LICENSED PRACTITIONER. UNINTERRUPTED USE OF HIGH CONCENTRATIONS OF OXYGEN OVER A LONG DURATION WITHOUT MONITORING ITS EFFECT ON OXYGEN CONTENT OF ARTERIAL BLOOD MAY BE HARMFUL. USE ONLY WITH PRESSURE REDUCING EQUIPMENT AND APPARATUS DESIGNED FOR OXYGEN. DO NOT REMOVE THIS PRODUCT LABEL. CAUTION: FEDERAL LAW PROHIBITS DISPENSING WITHOUT A PRESCRIPTION.

IN CASE OF FROSTBITE OBTAIN PROFESSIONAL MEDICAL TREATMENT IMMEDIATELY.

OXYGEN REFRIGERATED LABEL

OXYGEN U.S.P. REFRIGERATED LIQUID - OXYGEN UN 1073 PRODUCED BY AIR LIQUEFACTION

MARKETED BY BERNENS MEDICAL

WARNING: ALWAYS KEEP CONTAINER IN UPRIGHT POSITION. EXTREMELY COLD OXIDIZING LIQUID AND GAS UNDER PRESSURE. VIGOROUSLY ACCELERATES COMBUSTION. COMBUSTIBLES IN CONTACT WITH LIQUID OXYGEN MAY EXPLODE ON IGNITION OR IMPACT. CAN CAUSE SEVERE FROSTBITE. KEEP OIL, GREASE AND COMBUSTIBLES AWAY. USE ONLY WITH EQUIPMENT CLEANED FOR OXYGEN SERVICE. STORE AND USE WITH ADEQUATE VENTILATION. DO NOT GET LIQUID IN EYES, ON SKIN, OR CLOTHING. FOR LIQUID WITHDRAWAL WEAR FACE SHIELD AND GLOVES. DO NOT DROP OR HANDLE CONTAINER ROUGHLY. USE HAND TRUCK FOR CONTAINER MOVEMENT. AVOID SPILLS. DO NOT WALK ON OR ROLL EQUIPMENT OVER SPILLS. CLOSE VALVE AFTER EACH USE AND WHEN EMPTY. USE IN ACCORDANCE WITH COMPRESSED GAS ASSOCIATION PAMPHLETS G-4, G-4.1, G-4.4, P-1, P-12, AND P-14 AND WITH MATERIAL SAFETY DATA SHEET.

253